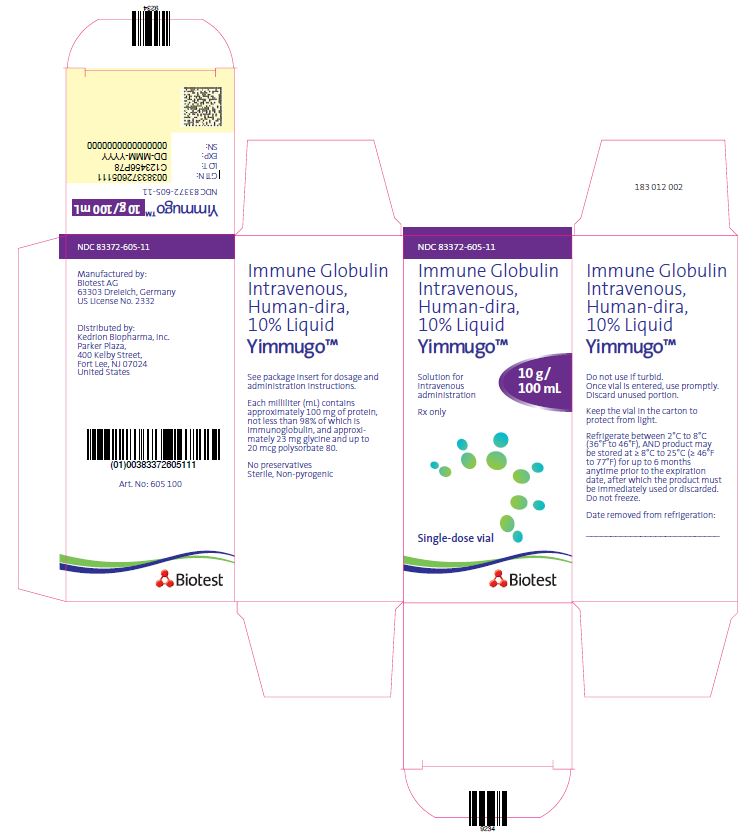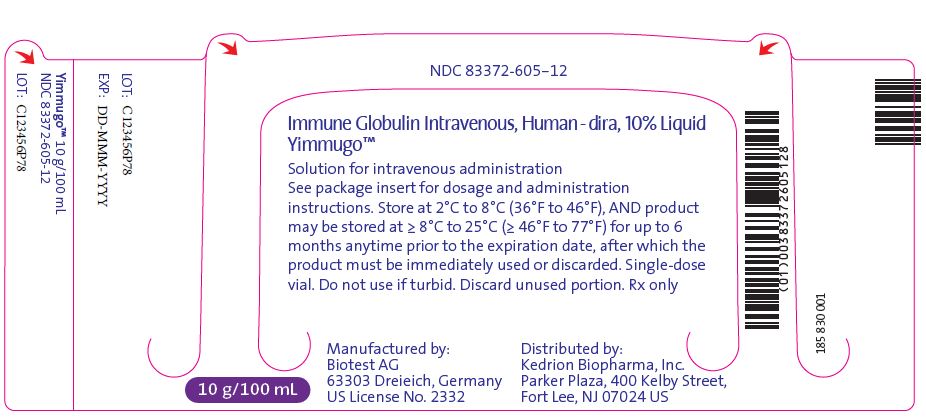 DRUG LABEL: YIMMUGO
NDC: 83372-605 | Form: SOLUTION
Manufacturer: Biotest AG
Category: other | Type: PLASMA DERIVATIVE
Date: 20240731

ACTIVE INGREDIENTS: HUMAN IMMUNOGLOBULIN G 10 g/100 mL
INACTIVE INGREDIENTS: GLYCINE; POLYSORBATE 80; WATER

HIGHLIGHTS OF PRESCRIBING INFORMATION

These highlights do not include all the information needed to use YIMMUGO safely and effectively. See full prescribing information for YIMMUGO.
YIMMUGO (immune globulin intravenous, human - dira), 10% liquid
Initial U.S. Approval: 2024

WARNING: THROMBOSIS, RENAL DYSFUNCTION and ACUTE RENAL FAILURE

See full prescribing information for complete boxed warning.

- Thrombosis may occur with immune globulin intravenous (IGIV) products, including YIMMUGO. (5.3)
- Renal dysfunction, acute renal failure, osmotic nephrosis, and death may occur with the administration of IGIV products in predisposed patients. Renal dysfunction and acute renal failure occur more commonly in patients receiving IGIV products containing sucrose. YIMMUGO does not contain sucrose. (5.4)
- For patients at risk of thrombosis, renal dysfunction or renal failure, administer YIMMUGO at the minimum dose and infusion rate practicable. Ensure adequate hydration in patients before administration. Monitor for signs and symptoms of thrombosis and assess blood viscosity in patients at risk for hyperviscosity. (2.1, 2.3, 5.3)

1 INDICATIONS AND USAGE

YIMMUGO is an immune globulin intravenous, human - dira, 10% liquid indicated for the treatment of primary humoral immunodeficiency (PI) in patients 2 years of age or older. (1)

2 DOSAGE AND ADMINISTRATION

Intravenous use only.
Dose | Infusion Number | Initial Infusion Rate | Maintenance Infusion Rate (if tolerated)
300–800 mg/kg (3–8 mL/kg) every 3–4 weeks | For the 1st infusion | 0.5 mg/kg/min (0.005 mL/kg/min) for 30 minutes | Gradually increase every 30 minutes up to 3.0 mg/kg/min (0.03 mL/kg/min).
300–800 mg/kg (3–8 mL/kg) every 3–4 weeks | From the 2nd infusion | 0.5 mg/kg/min (0.005 mL/kg/min) for 30 minutes | Gradually increase up to 13 mg/kg/min (0.13 mL/kg/min).

- Ensure that patients with pre-existing renal insufficiency are not volume depleted; consider discontinuing YIMMUGO if renal function deteriorates. (2.3, 5.4)
- For patients at risk of renal dysfunction or thrombotic events, administer YIMMUGO at the minimum dose and infusion rate practicable. (2.3, 5.4, 5.3)

3 DOSAGE FORMS AND STRENGTHS

YIMMUGO is a solution containing 10% IgG (100 mg/mL): 5 g in 50 mL, 10 g in 100 mL, 20 g in 200 mL. (3)

4 CONTRAINDICATIONS

- History of anaphylactic or severe systemic reaction to human immune globulin. (4)
- IgA-deficient patients with antibodies to IgA and a history of hypersensitivity. (4)

5 WARNINGS AND PRECAUTIONS

- IgA-deficient patients with antibodies to IgA are at greater risk of developing severe hypersensitivity and anaphylactic reactions to YIMMUGO. Epinephrine should be available for immediate treatment of severe acute hypersensitivity reactions. (5.1)
- Hemolysis, either intravascular or due to enhanced red blood cell sequestration can develop subsequent to YIMMUGO treatments. Risk factors include high doses and non-O blood group. Closely monitor patients for hemolysis and hemolytic anemia. (5.2)
- In patients at risk of developing acute renal failure, monitor renal function, including blood urea nitrogen (BUN) and serum creatinine, and urine output. (5.4)
- Hyperproteinemia, increased serum viscosity, and hyponatremia or pseudohyponatremia can occur in patients receiving IGIV treatment. (5.5)
- Aseptic meningitis syndrome (AMS) has been reported with IGIV treatments, especially with high doses or rapid infusion. (5.6)
- Monitor patients for pulmonary adverse reactions (transfusion-related acute lung injury [TRALI]). (5.7)
- YIMMUGO is made from human blood and may contain infectious agents, e.g., viruses, the variant Creutzfeldt-Jakob disease [vCJD] agent and, theoretically, the Creutzfeldt-Jakob disease (CJD) agent. (5.8)

6 ADVERSE REACTIONS

The most common adverse reactions in ≥5% of clinical trial patients were headache, upper respiratory tract infections, fatigue, nausea and increased blood pressure. (6.1)

To report SUSPECTED ADVERSE REACTIONS, contact Kedrion Biopharma Inc. at 1-855-3KDRION (1-855-353-7466) or FDA at 1-800-FDA-1088 orwww.fda.gov/medwatch.

7 DRUG INTERACTIONS

Passive transfer of antibodies may:

- Transiently interfere with the immune response to live virus vaccines, e.g. measles, mumps, rubella and varicella. (7.2)
- Interact with loop diuretics. (7.4)
- Confound the results of serological testing. (7.3, 5.10)

8 USE IN SPECIFIC POPULATIONS

Geriatric: In patients over age 65 who are at risk of developing thrombosis or renal insufficiency, infuse YIMMUGO at the minimum rate practicable and do not exceed the recommended dose. (8.5)

FULL PRESCRIBING INFORMATION

WARNING: THROMBOSIS, RENAL DYSFUNCTION and ACUTE RENAL FAILURE

- Thrombosis may occur with immune globulin intravenous (IGIV) products, including YIMMUGO [see Warnings and Precautions (5.3), Patient Counseling Information (17)].
- Renal dysfunction, acute renal failure, osmotic nephrosis, and death may occur with the administration of IGIV products in predisposed patients. Renal dysfunction and acute renal failure occur more commonly in patients receiving IGIV products containing sucrose. YIMMUGO does not contain sucrose [see Warnings and Precautions (5.4)] .
- For patients at risk of thrombosis, renal dysfunction or renal failure, administer YIMMUGO at the minimum dose and infusion rate practicable. Ensure adequate hydration in patients before administration. Monitor for signs and symptoms of thrombosis and assess blood viscosity in patients at risk for hyperviscosity [see Dosage and Administration (2.1, 2.3), Warnings and Precautions (5.3)] .

1 INDICATIONS AND USAGE

YIMMUGO (immune globulin intravenous, human – dira), is a 10% immune globulin liquid, indicated for the treatment of primary humoral immunodeficiency (PI) including but not limited to the humoral immune defect in congenital agammaglobulinemia, common variable immunodeficiency (CVID), X-linked agammaglobulinemia (XLA), Wiskott-Aldrich syndrome, and severe combined immunodeficiencies (SCID) in patients 2 years of age and older.

2 DOSAGE AND ADMINISTRATION

For intravenous use only.

2.1 Dosage

Table 1: Recommended Dosage and Administration
Dose | Infusion Number | Initial Infusion Rate | Maintenance Infusion Rate (if tolerated)
300–800 mg/kg (3–8 mL/kg) every 3–4 weeks | For the 1st infusion | 0.5 mg/kg/min (0.005 mL/kg/min) for 30 minutes | Gradually increase every 30 minutes up to 3.0 mg/kg/min (0.03 mL/kg/min).
300–800 mg/kg (3–8 mL/kg) every 3–4 weeks | From the 2nd infusion | 0.5 mg/kg/min (0.005 mL/kg/min) for 30 minutes | Gradually increase up to 13 mg/kg/min (0.13 mL/kg/min).

The dosage may be adjusted over time to achieve the desired trough levels and clinical response.

2.2 Preparation and Handling

- YIMMUGO is a clear to slightly opalescent, colorless to pale yellow solution. Inspect visually for particulate matter and discoloration prior to administration, whenever the solution and container permit. Do not use if the liquid is cloudy or turbid, discolored, or if it contains visible particulate matter.
- Do not shake.
- YIMMUGO should be at room or body temperature at the time of administration.
- Do not mix with other IGIV products or other intravenous medications.
- Do not dilute.
- YIMMUGO is for single use only. It contains no preservatives. Promptly use any vial that has been entered. Discard partially used vials and unused product in accordance with local requirements.
- Do not use YIMMUGO after expiration date on the product label [see How Supplied/Storage and Handling (16)].

2.3 Administration

Administer YIMMUGO at room temperature or body temperature by the intravenous route. Do not mix with any intravenously administered medications. For rate of infusion, refer to Table 1. Monitor patient vital signs throughout the infusion. Slow or stop the infusion if adverse reactions occur. If symptoms subside promptly, the infusion may be resumed at a lower rate that is comfortable for the patient.

Ensure that patients with pre-existing renal insufficiency are not volume depleted. For patients judged to be at risk for renal dysfunction or thrombotic events, administer YIMMUGO at the minimum infusion rate practicable, and consider discontinuation of administration if renal function deteriorates [see Boxed Warning, Warnings and Precautions (5.4, 5.3)].

Hydrate the patient adequately prior to the initiation of infusion.

3 DOSAGE FORMS AND STRENGTHS

YIMMUGO is a solution containing 10% IgG (100 mg/mL): 5 g in 50 mL, 10 g in 100 mL, 20 g in 200 mL.

4 CONTRAINDICATIONS

- YIMMUGO is contraindicated in patients who have had an anaphylactic or severe systemic reaction to the administration of human immune globulin.
- YIMMUGO is contraindicated in patients with IgA-deficiency who have antibodies against IgA and a history of hypersensitivity.

5 WARNINGS AND PRECAUTIONS

5.1 Hypersensitivity

Severe hypersensitivity reactions, including anaphylaxis, have been reported after YIMMUGO administration. [see Contraindications (4)]. In case of hypersensitivity, discontinue YIMMUGO infusion immediately and institute appropriate treatment. Epinephrine should be available for immediate treatment of severe acute hypersensitivity reactions.

YIMMUGO contains less than or equal to 300 micrograms per milliliter of IgA [see Description (11)]. Patients with known antibodies to IgA may have a greater risk of developing potentially severe hypersensitivity and anaphylactic reactions. YIMMUGO is contraindicated in IgA-deficient patients with antibodies against IgA and a history of hypersensitivity reaction [see Contraindications (4)].

5.2 Hemolysis

Hemolysis has been reported after YIMMUGO administration. IGIV products, including YIMMUGO, may contain blood group antibodies that can act as hemolysins and induce in vivocoating of red blood cells (RBCs) with immunoglobulin, causing a positive direct antiglobulin reaction and hemolysis.^1 Delayed hemolytic anemia can develop subsequent to IGIV treatment due to enhanced RBC sequestration, and acute hemolysis, consistent with intravascular hemolysis.The following risk factors may be associated with the development of hemolysis following IGIV administration: high doses (e.g. ≥2 g/kg given either as a single administration or divided over several days), and non-O blood group. Other individual patient factors, such as underlying inflammatory state (as may be reflected by elevated C-reactive protein or erythrocyte sedimentation rate), have been hypothesized to increase the risk of hemolysis following administration of IGIV, but their role is uncertain.

Monitor patients for clinical signs and symptoms of hemolysis [see Patient Counseling Information (17)] . If clinical signs and symptoms of hemolysis or a significant drop in hemoglobin or hematocrit are observed after YIMMUGO infusion, perform confirmatory laboratory testing. If transfusion is indicated for patients who develop hemolysis with anemia after receiving IGIV, perform cross-matching to avoid exacerbating ongoing hemolysis.

5.3 Thrombosis

Thrombosis may occur following treatment with immune globulin products,^2,^3 including YIMMUGO. Risk factors may include: advanced age, prolonged immobilization, hypercoagulable conditions, history of venous or arterial thrombosis, use of estrogens, indwelling central vascular catheters, hyperviscosity and cardiovascular risk factors. Thrombosis may occur in the absence of known risk factors.

Consider baseline assessment of blood viscosity in patients at risk for hyperviscosity, including patients with cryoglobulins, fasting chylomicronemia/markedly high triacylglycerols (triglycerides), or monoclonal gammopathies. For patients at risk of thrombosis, administer YIMMUGO at the minimum dose and infusion rate practicable. Ensure adequate hydration in patients before administration. Monitor for signs and symptoms of thrombosis and assess blood viscosity in patients at risk for hyperviscosity [see Boxed Warning, Dosage and Administration (2), Patient Counseling Information (17)] .

5.4 Renal Failure

Renal dysfunction, acute renal failure, osmotic nephropathy, and death may occur upon use of human IGIV products. Ensure that patients are not volume depleted before administering YIMMUGO. In patients who are at risk of developing renal dysfunction, because of pre-existing renal insufficiency or predisposition to acute renal failure (such as diabetes mellitus, hypovolemia, overweight, use of concomitant nephrotoxic drugs, or age of >65 years), administer YIMMUGO at the minimum infusion rate practicable [see Boxed Warning and Dosage and Administration (2.3)].

Conduct periodic monitoring of renal function and urine output in patients judged to be at increased risk of developing acute renal failure. Assess renal function, including measurement of blood urea nitrogen (BUN) and serum creatinine, before the initial infusion of YIMMUGO and at appropriate intervals thereafter. If renal function deteriorates, consider discontinuing YIMMUGO [see Patient Counseling Information (17)].

5.5 Hyperproteinemia, increased serum viscosity and hyponatremia

Hyperproteinemia, increased serum viscosity, and hyponatremia may occur in patients receiving IGIV treatment, including YIMMUGO. It is critical to clinically distinguish true hyponatremia from a pseudohyponatremia that is associated with or causally related to hyperproteinemia with concomitant decreased calculated serum osmolality or elevated osmolar gap, because treatment aimed at decreasing serum free water in patients with pseudohyponatremia may lead to volume depletion, a further increase in serum viscosity, and a possible predisposition to thromboembolic events.

5.6 Aseptic Meningitis Syndrome

Aseptic meningitis syndrome (AMS) may occur infrequently in patients following IGIV treatments, including YIMMUGO. AMS usually begins within several hours to 2 days following IGIV treatment. Discontinuation of IGIV treatment has resulted in remission of AMS within several days without sequelae.^4 AMS is characterized by the following signs and symptoms: severe headache, nuchal rigidity, drowsiness, fever, photophobia, painful eye movements, nausea, and vomiting [see Patient Counseling Information (17)] . Cerebrospinal fluid (CSF) studies frequently reveal pleocytosis up to several thousand cells per cubic millimeter, predominantly from the granulocytic series, and elevated protein levels up to several hundred mg/dL, but negative culture results. Conduct a thorough neurological examination on patients exhibiting signs and symptoms of AMS, including CSF studies, to rule out other causes of meningitis.

AMS may occur more frequently in association with high doses (2 g/kg) and/or rapid infusion of IGIV.

5.7 Transfusion-Related Acute Lung Injury

Noncardiogenic pulmonary edema [Transfusion-Related Acute Lung Injury (TRALI)] may occur in patients following IGIV treatment,^4 including YIMMUGO. TRALI is characterized by severe respiratory distress, pulmonary edema, hypoxemia, normal left ventricular function and fever. Symptoms typically appear within 1 to 6 hours following treatment.

Monitor patients for pulmonary adverse reactions. If TRALI is suspected immediately stop IGIV and perform appropriate tests for the presence of anti-neutrophil antibodies and anti-human leukocyte antigen (HLA) antibodies in both the product and the patient’s serum [see Patient Counseling Information (17)]. TRALI is a potentially life-threatening condition requiring immediate intensive-care-unit management. TRALI may be managed using oxygen therapy with adequate ventilatory support.

5.8 Transmissible Infectious Agents

Because YIMMUGO is made from human blood, it may carry a risk of transmitting infectious agents, e.g., viruses, the variant Creutzfeldt-Jakob disease (vCJD) and theoretically, the Creutzfeldt-Jakob disease (CJD) agent. This also applies to unknown or emerging viruses and other pathogens. The risk of infectious agent transmission has been reduced by screening plasma donors and by including virus inactivation as well as virus and prion removal steps in the manufacturing process of YIMMUGO.

All infections suspected by a physician possibly to have been transmitted by this product should be reported by the physician or other healthcare provider to Kedrion Biopharma Inc. at 1-855-3KDRION (1-855-353-7466). Discuss the risks and benefits of YIMMUGO use with patient before prescribing or administering this product. [see Patient Counseling Information (17)] .

5.9 Monitoring Laboratory Tests

- Periodic monitoring of renal function and urine output is particularly important in patients judged to be at increased risk of developing acute renal failure. Assess renal function, including measurement of BUN and serum creatinine, before the initial infusion of YIMMUGO and at appropriate intervals thereafter [see Warnings and Precautions (5.4)] .
- Consider baseline assessment of blood viscosity in patients at risk for hyperviscosity, including those with cryoglobulins, fasting chylomicronemia/markedly high triacylglycerols (triglycerides), or monoclonal gammopathies, because of the potentially increased risk of thrombosis [see Warnings and Precautions (5.3)] .
- If signs and/or symptoms of hemolysis are present after an infusion of YIMMUGO, perform appropriate laboratory testing for confirmation [see Warnings and Precautions (5.2)] .
- If TRALI is suspected, perform appropriate tests for the presence of anti-neutrophil antibodies and anti-HLA antibodies in both the product and the patient's serum [see Warnings and Precautions (5.7) ].

5.10 Interference with Laboratory Tests

After infusion of immunoglobulin, the transitory rise of the various passively transferred antibodies in the patient’s blood may yield positive serological testing results, with the potential for misleading interpretation. Passive transmission of antibodies to erythrocyte antigens (e.g., A, B, and D) may cause a positive direct or indirect antiglobulin (Coombs’) test.

6 ADVERSE REACTIONS

6.1 Clinical Trials Experience

Because clinical trials are conducted under widely varying conditions, adverse reaction rates observed in the clinical trials of a drug cannot be directly compared to rates in the clinical trials of another drug and may not reflect the rates observed in practice.

Primary humoral immunodeficiency (PI)
In an open-label, prospective, multicenter, multinational trial, the efficacy, safety, and pharmacokinetic properties of YIMMUGO as replacement therapy in patients with PI were investigated in 67 patients (including 12 children and 6 adolescents).^5,^6 Patients received a dose between 200 mg to 800 mg per kg body weight (bw) every 3 or 4 weeks, for a treatment period of approximately 12 months. The initial dose and dosage interval was consistent with the patient’s prestudy IGIV treatment [see Clinical Studies (14)].

There were two serious adverse events (SAEs) related to YIMMUGO, occurring in two patients: anaphylactic reaction, and severe neutropenia. Both SAEs led to discontinuation of YIMMUGO. One patient also had mild hemolysis and positive Coomb’s test.

Adverse reactions (AR) occurring in ≥5% of patients are presented in Table 2.

Table 2: Adverse Reactions* in ≥ 5% of Patients
Adverse Reaction MedDRA - Preferred Term | Number (%) of Patients with AR N = 67 | Number (%) of Infusions Ninf= 923
≥1 Adverse reaction | 39 (58) | 93 (10)
Headache | 13 (19) | 22 (2)
Upper respiratory tract infections | 8 (12) | 8 (<1)
Fatigue | 5 (8) | 8 (<1)
Nausea | 4 (6) | 5 (<1)
Increased blood pressure | 4 (6) | 4 (<1)

* Adverse reactions were identified as all AEs that were temporally associated with an infusion (occurred during infusion or within 72 h after the end of an infusion) or that were assessed as related.

6.2 Postmarketing Experience

Because adverse reactions are reported voluntarily from a population of uncertain size, it is not always possible to reliably estimate their frequency or establish a causal relationship to drug exposure. The following adverse reactions have been identified and reported during the post-approval use of IGIV products:

- Respiratory: Apnea, Acute Respiratory Distress Syndrome (ARDS), TRALI, respiratory failure, hypoxemia, pulmonary edema, dyspnea, wheezing, cough, bronchospasm, pulmonary embolism.
- Cardiovascular: Cardiac arrest, thromboembolism, vascular collapse, hypotension, phlebitis, pallor, angina, tachycardia, bradycardia, palpitations, myocardial infarction, cyanosis.
- Neurological: Coma, loss of consciousness, seizures, (acute) encephalopathy, tremor, aseptic meningitis syndrome, migraine, speech disorder, paresthesia, hypoesthesia, photophobia.
- Integumentary: Stevens-Johnson syndrome, epidermolysis, erythema multiforme, bullous dermatitis, eczema, erythematous rash, dermatitis, pruritus, alopecia, urticaria.
- Gastrointestinal: Hepatic dysfunction, abdominal pain, diarrhea.
- Renal: Acute renal failure, osmotic nephropathy, renal pain.
- Hematologic: Pancytopenia, leukopenia, hemolysis.
- Musculoskeletal: Musculoskeletal pain, muscle spasm, arthralgia, myalgia, muscle stiffness.
- General disorders and administration site conditions: Pyrexia, rigors, injection-site reactions, chills, flushing, lethargy, malaise, burning sensation.
- Psychiatric disorders: Confusion, anxiety, agitation, nervousness.
- Metabolic and nutritional: Fluid overload, (pseudo) hyponatremia.
- Immune system disorders: Hypersensitivity (e.g. anaphylaxis, allergic reaction), angioedema.
- Investigations: Falsely elevated erythrocyte sedimentation rate, positive direct antiglobulin (Coombs’) test, increased hepatic enzymes.

7 DRUG INTERACTIONS

7.1 Intravenous Products

Clinical studies have not evaluated mixture of YIMMUGO (immune globulin intravenous, human-dira) with other intravenous drugs and solutions. Administer YIMMUGO separately from other drugs or medications which the patient may be receiving. Do not mix YIMMUGO with other IGIVs products.

7.2 Live Virus Vaccines

Immunoglobulin administration may transiently impair the efficacy of live attenuated virus vaccines such as measles, mumps, rubella, and varicella because the continued presence of high levels of passively acquired antibody may interfere with an active antibody response.^7 Inform the immunizing physician of recent therapy with YIMMUGO so that appropriate measures may be taken [see Patient Counseling Information (17)].

7.3 Serological Testing

Various passively transferred antibodies in immunoglobulin preparation may lead to misinterpretation of the results of serological testing.

7.4 Loop Diuretics

Avoid concomitant use of loop diuretics. Concomitant use of loop diuretics with IGIV may additionally contribute to an increased blood viscosity and subsequently increase the risk of thromboembolic events.

8 USE IN SPECIFIC POPULATIONS

8.1 Pregnancy

Risk Summary
No human data are available to indicate the presence or absence of drug-associated risk. Animal reproduction studies have not been conducted with YIMMUGO. It is not known whether YIMMUGO can cause fetal harm when administered to a pregnant woman or can affect reproduction capacity. Immune globulins cross the placenta from maternal circulation increasingly after 30 weeks of gestation. In the U.S. general population, the estimated background risk of major birth defects and miscarriage in clinically recognized pregnancies is 2-4% and 15-20% respectively. YIMMUGO should be given to pregnant women only if clearly needed.

8.2 Lactation

Risk Summary
No human data are available to indicate the presence or absence of drug-associated risk. Immune globulins are excreted into human milk. The developmental and health benefits of breast feeding should be considered along with the mother’s clinical need for YIMMUGO and any potential adverse effects on the breast-fed infant from YIMMUGO or from the underlying maternal condition.

8.4 Pediatric Use

YIMMUGO was evaluated in 18 pediatric patients (12 children age 2 to less than 12 years and 6 adolescents age 12 – 16 years) with PI. Dose requirements did not differ between children and adults. Safety and effectiveness has not been studied in pediatric patients with PI who are under the age of 2 years [see Clinical Studies (14)].

8.5 Geriatric Use

Clinical studies of YIMMUGO did not include sufficient numbers of patients aged 65 and over to determine whether they respond differently from younger patients. Other reported clinical experience has not identified differences in responses between the elderly and younger patients. In general, dose selection for an elderly patient should be cautious, usually starting at the low end of the dosing range, reflecting the greater frequency of decreased hepatic, renal, or cardiac function, and of concomitant disease or other drug therapy [see Boxed Warning, Warnings and Precautions (5.4, 5.3)] . Do not exceed recommended doses, and administer YIMMUGO at the minimum infusion rate practicable.

10 OVERDOSAGE

Overdose may lead to fluid overload and hyperviscosity. Patients at risk of complications of fluid overload and hyperviscosity include infants, elderly patients and those with cardiac or renal impairment.

11 DESCRIPTION

YIMMUGO, immune globulin intravenous, human – dira, is a highly purified, sterile, non-pyrogenic, ready-to-use 10% liquid preparation of concentrated polyclonal human immune globulin G (IgG) antibodies for intravenous administration. The product is a clear to slightly opalescent liquid, which is colorless to pale yellow. The active ingredient is human IgG purified from human Source Plasma and processed using a combination of cold ethanol fractionation, caprylic acid precipitation, as well as anion and cation exchange chromatography. YIMMUGO contains 100 ± 10 mg/mL protein, of which not less than 96% is IgG. The distribution of IgG subclasses is similar to that of normal plasma. YIMMUGO is formulated in water for injection containing 0.27 to 0.33 mmol/mL glycine, 2 to 20 mcg/mL polysorbate 80, with pH 4.4 to 5.2 and osmolality ranges of 280 to 380 mOsmol/kg. YIMMUGO contains not more than 300 mcg/mL of IgA. YIMMUGO does not contain carbohydrate stabilizers (e.g., sucrose, maltose) or preservatives.

YIMMUGO is prepared from pooled plasma obtained from healthy volunteer donors. Each plasma donation used for the manufacture of YIMMUGO is collected from FDA-licensed facilities. Plasma donations must test negative for hepatitis B virus (HBV) surface antigen (HBsAg), antibodies to human immunodeficiency virus (HIV) strains 1 and 2 (anti-HIV-1/2), and antibodies to the hepatitis C virus (anti-HCV) as determined by enzyme immunoassay (EIA). In addition, samples from manufacturing pools must test non-reactive for HIV RNA, HCV RNA, HBV DNA and Hepatitis A Virus (HAV) RNA, by Nucleic Acid Amplification Testing (NAT). Parvovirus B19 (B19V) DNA is also tested by NAT and must not exceed 10^4 IU/mL in the manufacturing pool.

The manufacturing process of YIMMUGO employs several steps to remove/inactivate adventitious viruses to further increase the margins of safety. These steps include caprylic acid, low pH treatment, anion exchange chromatography (AEX) and nanofiltration. Virus clearance studies with a scaled-down process have been performed for these steps to determine their capacity to inactivate or remove both enveloped and non-enveloped viruses. The results are shown in Table 3.

Table 3: Virus Clearance Data (Log10) for YIMMUGO for enveloped (HIV, BVDV, PRV) and non-enveloped viruses (HAV, EMCV, B19V, PPV, HEV)
Test Virus → ↓ Step | HIV | BVDV | PRV | HAV | EMCV | B19V* | PPV | HEV*
Caprylic Acid Treatment | ≥ 5.64 | ≥ 5.97 | ≥ 6.21 | ≥ 4.39 | n.d. | 2.48 | 1.01 | ≥ 4.96
Low pH Treatment | ≥ 6.63 | < 1 | n.d. | n.d. | n.d. | n.d. | < 1 | n.d.
Anion Exchange Chromatography | n.d. | 2.62 | n.d. | ≥ 3.95 | n.d. | ≥ 5.86 | 3.21 | n.d.
Virus Filtration | ≥ 4.72 | ≥ 4.72 | n.d. | ≥ 4.37 | ≥ 4.93 | ≥ 4.33 | 6.12 | n.d.
Total Virus Clearance† | ≥ 16.99 | ≥ 13.31 | ≥ 6.21 | ≥ 12.71 | ≥ 4.93 | ≥ 12.67 | 10.34 | ≥ 4.96

n.d. not determined.
* Polymerase chain reaction (PCR) was used to quantify B19V and HEV genome counts (all other viruses were quantified by in-vitro infectivity assays, using mammalian cell lines).
† Log10 reduction factors of 1 or smaller were not considered for calculation of total virus clearance.
BVDV, bovine viral diarrhea virus, a model for hepatitis C virus; PRV, pseudorabies virus, a model for hepatitis B virus;

EMCV, encephalomyocarditis virus, a model for hepatitis A virus; B19V, parvovirus B19;
PPV, porcine parvovirus, a model for B19V; HEV, hepatitis E virus.

The manufacturing process was also investigated for its capacity to decrease the infectivity of an experimental agent of transmissible spongiform encephalopathy (TSE), considered a model for CJD and its variant vCJD. Several of the production steps have been shown to decrease TSE infectivity of the experimental model agent. TSE reduction steps include caprylic acid treatment followed by depth filtration (in sequence, a total of ≥ 5.99 log10). These studies provide reasonable assurance that low levels of vCJD/CJD agent infectivity, if present in the starting material, would be removed.

12 CLINICAL PHARMACOLOGY

12.1 Mechanism of Action

YIMMUGO provides a broad spectrum of opsonizing and neutralizing immune globulin G (IgG) antibodies against a wide variety of pathogens and their toxins, which helps to avoid recurrent serious opportunistic infections. The mechanism of action has not been fully elucidated but may include immunomodulatory effects.

12.2 Pharmacodynamics

YIMMUGO contains mainly IgG with a broad spectrum of antibodies against various infectious agents, reflecting the IgG activity found in the donor population. YIMMUGO which is prepared from pooled plasma from not less than 1,000 donors, has an IgG subclass distribution similar to that of native human plasma. Adequate doses of IGIV can restore an abnormally low IgG level to the normal range. Standard pharmacodynamics studies were not performed.

12.3 Pharmacokinetics

The pharmacokinetic parameters for YIMMUGO were determined in an open-label, prospective, multicenter, multinational clinical trial in 57 patients with PI [see Clinical Studies (14)] . IgG levels for determination of PK parameters were measured after the 7th (3-week schedule, n = 10) or 5th infusion (4-week schedule, n = 47) in 57 patients (6 to <76 years of age). Patients for whom PK data was available received doses of YIMMUGO between 280 mg/kg to 800 mg/kg. The mean half-life of YIMMUGO for adults was 24.8–29.9 days depending on the treatment schedule (see Table 4). PK parameters did not indicate any clinically relevant differences between the 3-week and 4-week schedule.

Table 4: Pharmacokinetic Parameters of YIMMUGO at Steady State

a) PK Parameters: 3 Week Schedule - Mean (SD)
Parameter | 6-<12 Years | 12-<17 Years | 17-<76 Years
N* | 2 | 1 | 7
Cmax(mg/mL) | 19.6 (3.9) | 34.8 | 32.3 (6.3)
Ctrough(mg/mL) | 8.2 (0.2) | 13 | 10.4 (2.4)
AUCtau(day × g/L) | 238.7 (5.9) | 477 | 398.4 (99)
CLss(mL/day/kg) | 2 (0.3) | 1.2 | 1.4 (0.3)
Vss(mL/kg) | 69.4 (23) | 27 | 53.5 (15.7)
Half-life (days) | 29.5, n=1 | 15.5 | 24.8 (5.1), n=5

b) PK Parameters: 4 Week Schedule - Mean (SD)
Parameter | 6-<12 Years | 12-<17 Years | 17-<76 Years
N* | 3 | 5 | 39
Cmax(mg/mL) | 24.7 (1.2), n=2 | 22.2 (2.3), n=4 | 27.1 (6.3)
Ctrough(mg/mL) | 7.1 (1.2), n=3 | 9.1 (1.7), n=5 | 8.1 (2.5)
AUCtau(day × g/L) | 392.1 (19.7), n=2 | 415.1 (94.9), n=4 | 397 (103.6), n=36
CLss(mL/day/kg) | 1 (0.1), n=2 | 0.9 (0.3), n=4 | 1.3 (0.5), n=36
Vss(mL/kg) | 74.6 (7.2), n=2 | 56.5 (12.8), n=4 | 61.8 (39.1), n=35
Half-life (days) | 57.5, n=1 | 31.7 (3), n=2 | 29.9 (12.4), n=22

* Divergent number of subjects for individual PK parameters are indicated behind values.

Abbreviations: AUCtau= area under the concentration-time curve calculated from start to end of the dosing interval; CLss= clearance at steady state; Cmax= maximum serum concentration; Ctrough= trough concentration at steady state; n = number of subjects with data; SD = standard deviation; Vss= volume of distribution at steady state

Although no systematic study was conducted to evaluate the effect of sex on the pharmacokinetics of YIMMUGO, subgroup analysis between males (n= 37) and females (n = 30) revealed no clinically relevant differences in exposure and IgG trough levels.

13 NONCLINICAL TOXICOLOGY

13.1 Carcinogenesis, Mutagenesis, Impairment of Fertility

No animal studies were conducted to evaluate the carcinogenic or mutagenic effects of YIMMUGO or its effects on fertility.

13.2 Animal Toxicology and/or Pharmacology

A single dose toxicology study in male and female Sprague Dawley rats was conducted. Study endpoints included clinical and hematological evaluations, post-mortem analyses, and sensory-motor activity evaluations on days 1 and 15 post-dosing. Under the conditions of this study, the single intravenous infusion administration of YIMMUGO at a dose level of 2 g/kg body weight given at a rate of 20 mL/kg for 40 minutes was not associated with any adverse findings.

14 CLINICAL STUDIES

Trial 991(NCT02810444): The safety, effectiveness and pharmacokinetics of YIMMUGO as replacement therapy in patients with PI were investigated in an open-label, prospective, multicenter, multinational trial. The study planned to enroll patients 2 to 75 years of age with PI who had established IGIV therapy for at least 3 months with a constant dose, and at least one IgG trough level of ≥5g/L during the previous 3 months. The patients were to receive YIMMUGO at doses between 0.2 to 0.8 g per kg body weight (bw) at either 3-week (Q3W) or 4-week (Q4W) intervals for a period of 12 months. The initial dose and dosage interval had to be consistent with the subject’s prestudy IGIV treatment and doses were to be adjusted for changes in weight or as medically indicated.

The primary efficacy outcome measure was the rate of serious bacterial infections (SBI), defined as bacterial pneumonia, bacteremia/septicemia, osteomyelitis/septic arthritis, visceral abscesses, or bacterial meningitis over a period of 12 months. The predefined success criteria was demonstration of rate of less than one acute SBI per patient per year. Additional efficacy outcome measures included occurrence of any infection, time to resolution of infections, use of antibiotics, the number of days missed from work/school, and hospitalizations.

The trial enrolled 67 patients with a mean age of 35 years (range 2 to 74 years). There were 18 pediatric patients (including 12 children and 6 adolescents), and 5 patients ≥65 years of age. The study population was mainly white (n=66; 98.5%) and males represented 55% (n=37). The most common underlying cause of PI was CVID (n=53; 79%). Other etiologies included XLA (n=10; 15%), congenital agammaglobulinaemia (n=2; 3%), congenital hypogammaglobulinaemia (n=1; 1.5%), and specific antibody defect (n=1; 1.5%).

Patients received a dose ranging from 200 mg to 833 mg per kg body weight (bw) every 3 (n=12) or 4 weeks (n=55), for a treatment period of approximately 12 months. Infusions were initiated at a rate of 0.5 mg/kg/min (0.005 mL/kg/min) for the first 30 minutes, and, if tolerated, could be increased to a maximum tolerated rate not exceeding 13 mg/kg/min (0.13mL/kg/min). During the study 10 patients required a dose adjustment (increase) due to low IgG levels (including 7 patients who had trough levels <5 g/L). Additionally, 2 patients required dose adjustment (increase) due to infections, and 1 patient required a dose reduction due to an adverse reaction (worsening of fatigue).

The study demonstrated that treatment with YIMMUGO resulted in less than one SBI per person-year. A total of five acute SBIs occurred among study participants. All five acute SBIs were bacterial pneumonia. A summary of efficacy outcomes is shown in Table 5.

Table 5: Summary of Efficacy Results in Trial 991
Category | Results
Number of Patients | 67 patients with 67.6 years on study
Infections
Annualized rate of acute SBIs | 0.07 acute SBIs/person-year (99% CI 0.21)
Annualized rate of other infections | 2.7 infections/person-year
Time to resolution of infection* | 7 (1, 172) days†
Antibiotics
Number of patients with therapeutic antibiotic use | 35 subjects (52.2%)
Number of days on therapeutic antibiotics* | 9.5 (3, 35) days
Time lost from work/school
Number of patients who lost ≥1 day due to infection | 26 subjects (38.8%)
Number of days lost from work/school due to infection* | 6 (1, 85) days
Hospitalizations due to infection
Number of patients with hospitalizations due to infection | 3 subjects (4.5%)
Number of days hospitalized* | 2 (2, 20) days
Annualized rate of hospitalization due to infection | 0.36 days/person-year

* Number of days presented in median (min, max) among patients with events of a duration of ≥1 day; maximum duration was used if there were multiple events.

† Two patients had unresolved infections at the last follow-up visit.

15 REFERENCES

1. Bellac, CL, Hottiger T, Jutzi MP, Bögli-Stuber K, Sänger M, Hanschmann K-M, et al. The role of isoagglutinins in intravenous immunoglobulin-related hemolysis. Transfusion 2015;55 Suppl 2:S13-22.
2. Dalakas, MC. High-dose intravenous immunoglobulin and serum viscosity: risk of precipitating thromboembolic events. Neurology 1994;44:223-6.
3. Wolberg AS, Kon RH, Monroe DM, Hoffman M. Coagulation factor XI is a contaminant in intravenous immunoglobulin preparations. Am J Hematol 2000;65:30-4.
4. Guo, Y, Tian X, Wang X,Xiao Z.Adverse effects of immunoglobulin therapy. Front Immunol 2018;9:1299.
5. Kriván G, Borte M, Harris JB, Lumry WR, Aigner S, Lentze S, et al. Efficacy, safety and pharmacokinetics of a new 10% normal human immunoglobulin for intravenous infusion, BT595, in children and adults with primary immunodeficiency disease. Vox Sang 2022;117:1153-62.
6. Kriván G, Borte M, Soler‑Palacin P, Church JA, Csurke I, Harris JB, et al. BT595, a 10% human normal immunoglobulin, for replacement therapy of primary immunodeficiency disease: results of a subcohort analysis in children. J Clin Immunol 2023;43:557-67.
7. Siber GA, Werner BG, Halsey NA, Reid R, Almeido-Hll J, Garrett SC, et al. Interference of immune globulin with measles and rubella immunization. J Pediatr 1993;122:204-11.

16 HOW SUPPLIED/STORAGE AND HANDLING

YIMMUGO is supplied in 5, 10 and 20 gram single-dose vials.

Package NDC | Container NDC | Size | Gram Protein
83372-605-01 | 83372-605-02 | 50 mL | 5
83372-605-11 | 83372-605-12 | 100 mL | 10
83372-605-21 | 83372-605-22 | 200 mL | 20

- The components used in the packaging for YIMMUGO are not made with natural rubber latex.
- Keep YIMMUGO in its original carton to protect it from light.
- Refrigerate between 2°C to 8°C (36°F to 46°F).
- Do not use after expiration date.
- Within the expiration date, the product may be stored at room temperature (more than 8°C and up to 25°C/ more than 46°F and up to 77°F) for a single period not exceeding 6 months. Once the product has been taken out of the refrigerator, it must not be returned to the refrigerator. Please record the date of the beginning of storage at room temperature on the product carton.
- Do not freeze. Do not use any solutions that have been frozen.

17 PATIENT COUNSELING INFORMATION

Inform patients of the early signs of hypersensitivity reactions to YIMMUGO (including hives, generalized urticaria, tightness of the chest, wheezing, hypotension, and anaphylaxis), and advise them to notify their physician if they experience any of these symptoms [see Warnings and Precautions (5.1)] .

Instruct patients taking YIMMUGO to immediately report symptoms of:

- Acute Renal Dysfunction and Acute Renal Failure which may include decreased urine output, sudden weight gain, fluid retention/edema, and/or shortness of breath. Such symptoms may suggest kidney damage [see Boxed Warning, Warnings and Precautions (5.4)].
- Thrombosis which may include pain and/or swelling of an arm or legs/feet with warmth over the affected area, discoloration of an arm or leg, unexplained shortness of breath, acute chest pain or discomfort that worsens on deep breathing, unexplained rapid pulse, numbness or weakness on one side of the body [see Warning and Precaution (5.3)] .
- Aseptic Meningitis Syndrome (AMS) which may include severe headache, neck stiffness, drowsiness, fever, sensitivity to light, painful eye movements, nausea and vomiting [see Warnings and Precautions (5.6)] .
- Hemolysis which may include fatigue, increased heart rate, yellowing of skin or eyes, dark- colored urine [see Warnings and Precautions (5.2)] .
- Transfusion-Related Acute Lung Injury (TRALI) which includes trouble breathing, chest pain, blue lips or extremities, fever [see Warnings and Precautions (5.7)] .

Inform patients that YIMMUGO:

- Is made from human plasma and may contain infectious agents that can cause disease (e.g., viruses, and theoretically, the CJD agent). While the risk that YIMMUGO can transmit an infection has been reduced by screening plasma donors for prior exposure, testing donated plasma, and inactivating or removing certain viruses during manufacturing, patients should report any symptoms that concern them [see Description (11) and Warnings and Precautions (5.8)] .
- Can interfere with their immune response to live virus vaccines (e.g., measles, mumps, rubella, and varicella). Instruct patients to notify their healthcare professional of this potential interaction when they are receiving vaccinations [see Drug Interactions (7.2)] .

Manufactured by:
Biotest AG
63303 Dreieich, Germany
U.S. license no. 2332

Distributed by:
Kedrion Biopharma, Inc.
Parker Plaza, 400 Kelby Street,
Fort Lee, NJ 07024 United States

PACKAGE LABEL

NDC 83372-605-11
Immune Globulin
Intravenous,
Human - dira,
10% Liquid
Yimmugo ™10 g/100 mL
Solution for
intravenous
administration
Rx only
Single-dose vial
Biotest
See package insert for dosage and
administration instructions.
Each milliliter (mL) contains
approximately 100 mg of protein,
not less than 98% of which is
immunoglobulin, and approximately
23 mg glycine and up to
20 mcg polysorbate 80.
No preservatives
Sterile, Non-pyrogenic
Do not use if turbid.
Once vial is entered, use promptly.
Discard unused portion.
Keep the vial in the carton to
protect from light.
Refrigerate between 2°C to 8°C
(36°F to 46°F), AND product may
be stored at ≥ 8°C to 25°C (≥ 46°F
to 77°F) for up to 6 months
anytime prior to the expiration
date, after which the product must
be immediately used or discarded.
Do not freeze.
Date removed from refrigeration:
Manufactured by:
Biotest AG
63303 Dreieich, Germany
US License No. 2332

Distributed by:
Kedrion Biopharma, Inc.
Parker Plaza,
400 Kelby Street,
Fort Lee, NJ 07024
United States

Art. No: 605 100

GTIN: 00383372605111

LOT: C123456P78
EXP: DD-MMM-YYYY
SN: 0000000000000000

NDC 83372-605-12
Immune Globulin Intravenous, Human - dira, 10% Liquid
Yimmugo™
Solution for intravenous administration
See package insert for dosage and administration
instructions. Store at 2°C to 8°C (36°F to 46°F), AND product
may be stored at ≥ 8°C to 25°C (≥ 46°F to 77°F) for up to 6
months anytime prior to the expiration date, after which the
product must be immediately used or discarded. Single-dose
vial. Do not use if turbid. Discard unused portion. Rx only
10 g/100 mL
Manufactured by:
Biotest AG
63303 Dreieich, Germany
US License No. 2332

Distributed by:
Kedrion Biopharma, Inc.
Parker Plaza,
400 Kelby Street,
Fort Lee, NJ 07024 US

LOT: C123456P78
EXP: DD-MMM-YYYY

Yimmugo™10 g/100 mL
NDC 83372-605-12
LOT: C123456P78
185 830 001